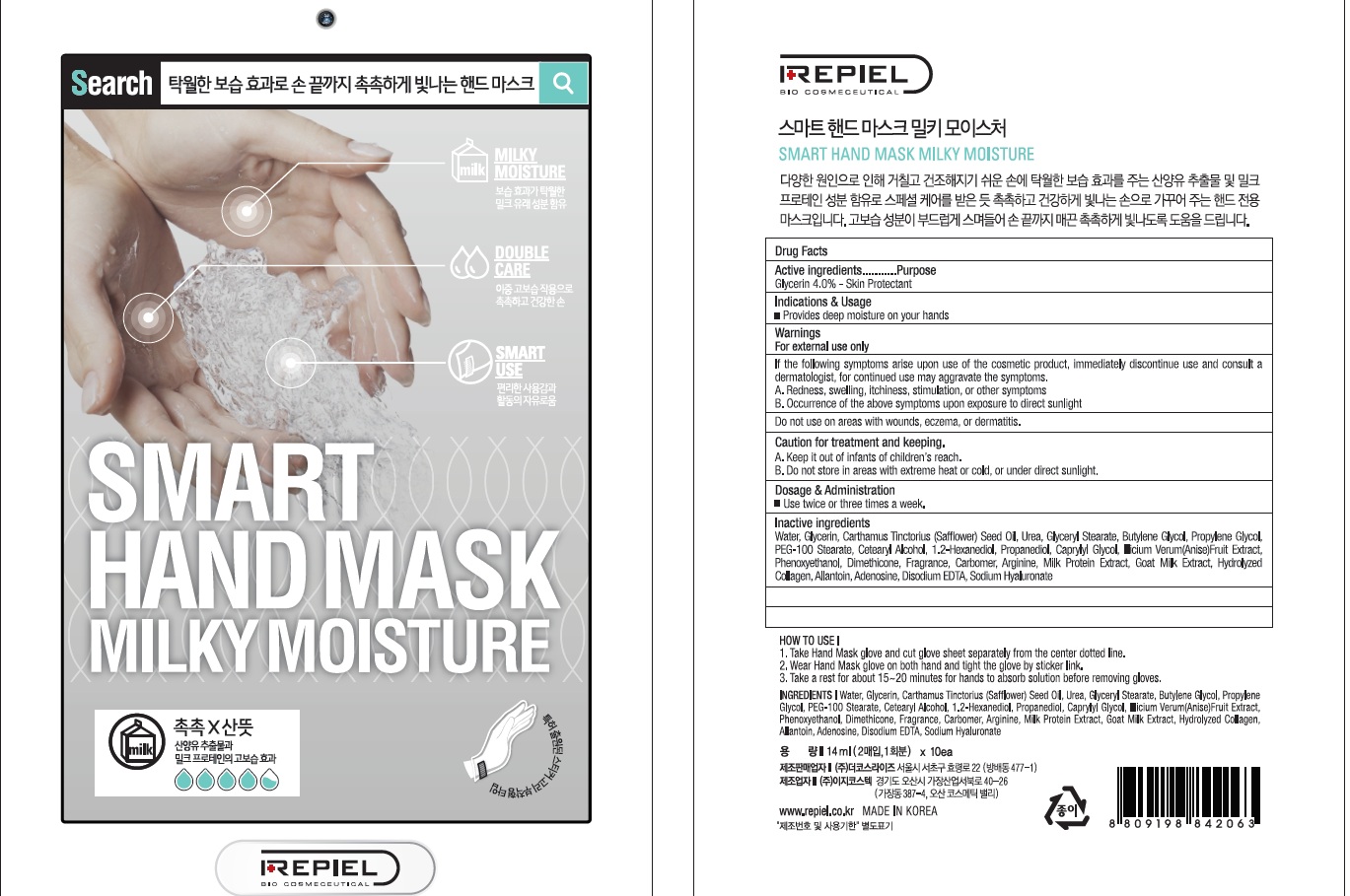 DRUG LABEL: REPIEL SMART HAND MASK MILKY MOISTURE
NDC: 70758-030 | Form: PATCH
Manufacturer: THE COSRISE CO.,LTD
Category: otc | Type: HUMAN OTC DRUG LABEL
Date: 20160629

ACTIVE INGREDIENTS: Glycerin 0.56 g/14 mL
INACTIVE INGREDIENTS: Water; Butylene Glycol

ACTIVE INGREDIENT

Active Ingredient: Glycerin 4.0%

INACTIVE INGREDIENT

Inactive Ingredients: Water, Carthamus Tinctorius (Safflower) Seed Oil, Urea, Glyceryl Stearate, Butylene Glycol, Propylene Glycol, PEG-100 Stearate, Cetearyl Alcohol, 1.2-Hexanediol, Propanediol, Caprylyl Glycol, Illicium Verum(Anise)Fruit Extract, Phenoxyethanol, Dimethicone, Fragrance, Carbomer, Arginine, Milk Protein Extract, Goat Milk Extract, Hydrolyzed Collagen, Allantoin, Adenosine, Disodium EDTA, Sodium Hyaluronate

PURPOSE

Purpose: Skin Protectant

WARNINGS

Warnings: For external use only. 1. If the following symptoms arise upon use of the cosmetic product, immediately discontinue use and consult a dermatologist, for continued use may aggravate the symptoms. A. Redness, swelling, itchiness, stimulation, or other symptoms B. Occurrence of the above symptoms upon exposure to direct sunlight. 2. Do not use on areas with wounds, eczema, or dermatitis. 3. Caution for treatment and keeping. A. Keep it out of infants of children’s reach. B. Do not store in areas with extreme heat or cold, or under direct sunlight.

KEEP OUT OF REACH OF CHILDREN

Keep it out of infants of children's reach.

INDICATIONS & USAGE

Indications & Usage: Provides deep moisture on your hands

How to use: 1. Take Hand Mask glove and cut glove sheet separately from the center dotted line. 2. Wear Hand Mask glove on both hand and tight the glove by sicker link. 3. Take a rest for about 15~20 minutes for hands to absorb solution before removing gloves.

DOSAGE & ADMINISTRATION

Dosage & Administration: Use twice or three times a week.